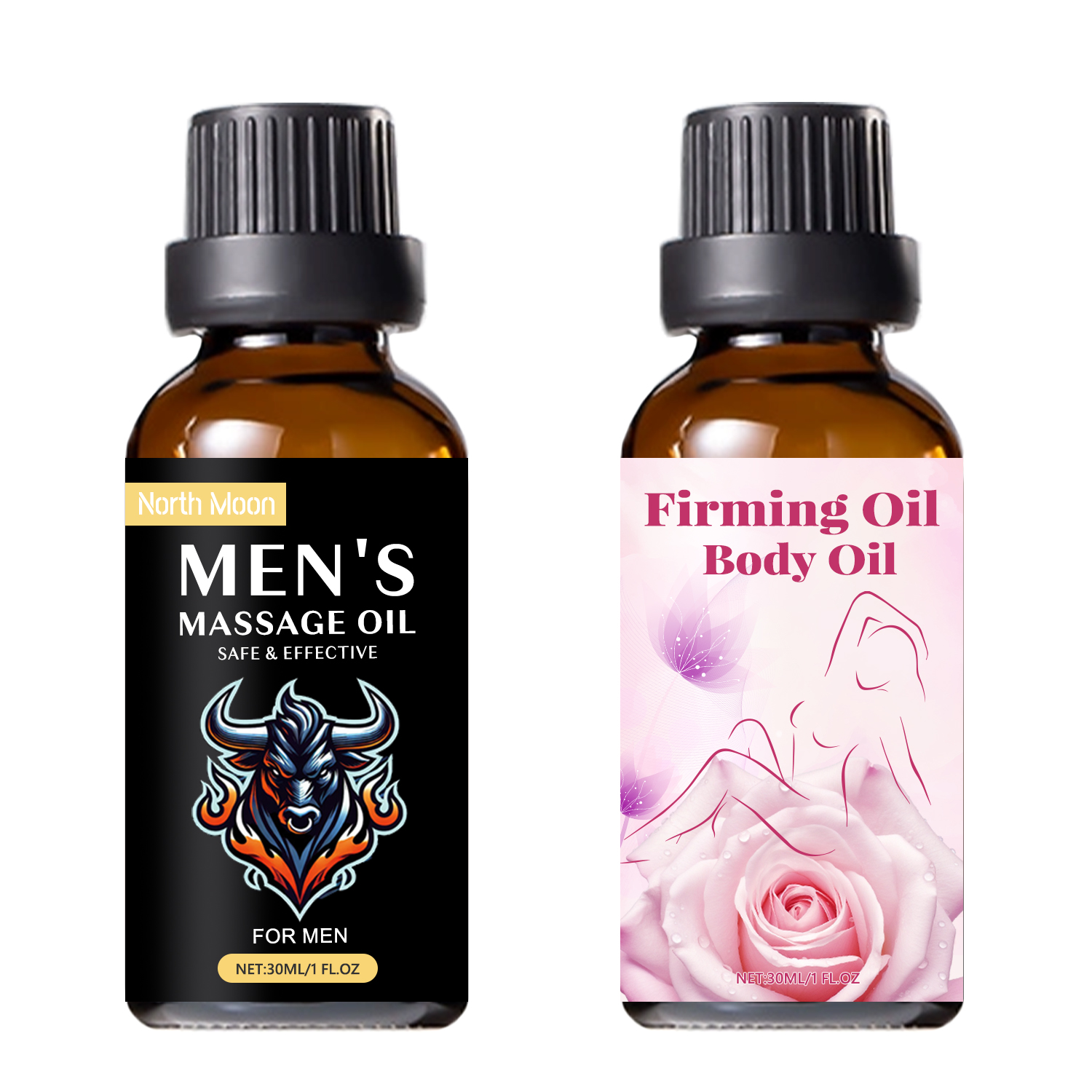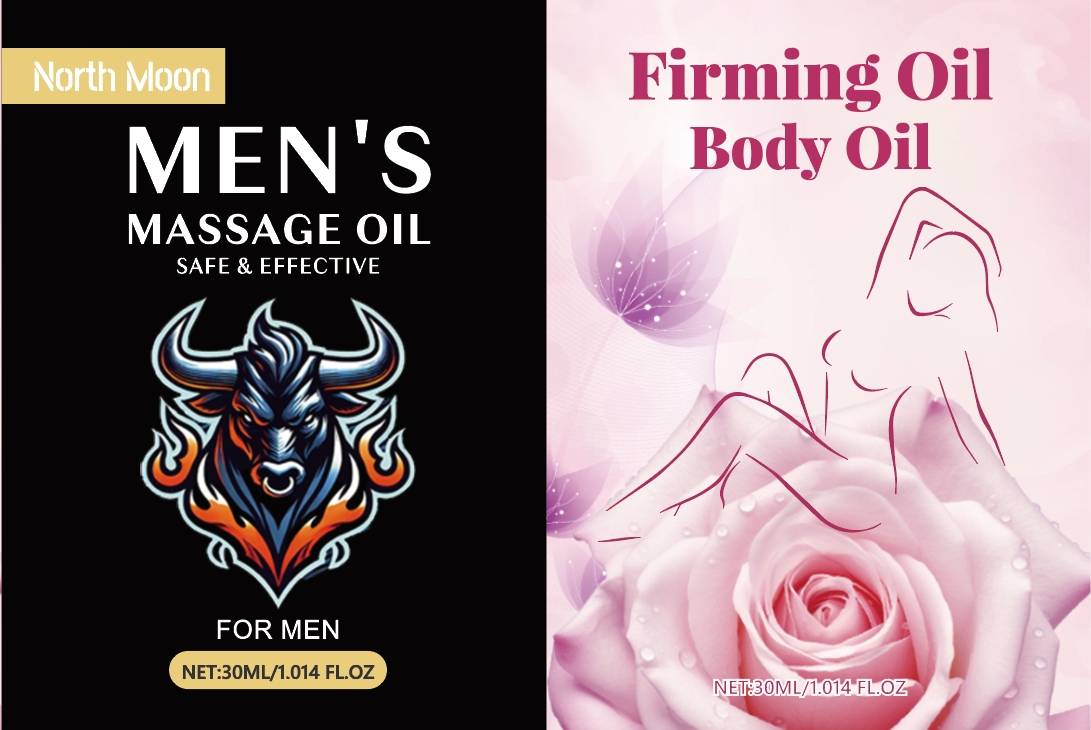 DRUG LABEL: Mens massage Oil
NDC: 84025-210 | Form: OIL
Manufacturer: Guangzhou Yanxi Biotechnology Co., Ltd
Category: otc | Type: HUMAN OTC DRUG LABEL
Date: 20241012

ACTIVE INGREDIENTS: PANTHENOL 3 mg/100 mL; GLYCERIN 5 mg/100 mL
INACTIVE INGREDIENTS: WATER

DOSAGE AND ADMINISTRATION

Simply wash the penis, apply and gently massage until absorbed. It will work for a short time.

WARNINGS

Keep out of children

INACTIVE INGREDIENT

Aqua

INDICATIONS AND USAGE

Sexual delay - This product penis massage oil can promote sexual desire, recover quickly after sexual intercourse, obtain more sexual pleasure and orgasm, delay sexual life, and prolong penile erection time.

keep out of children

PURPOSE

Bigger and longer penis - Penile erectile cream can make the penis thicker, bigger and longer. It can help you increase feelings of desire and enhance orgasm.